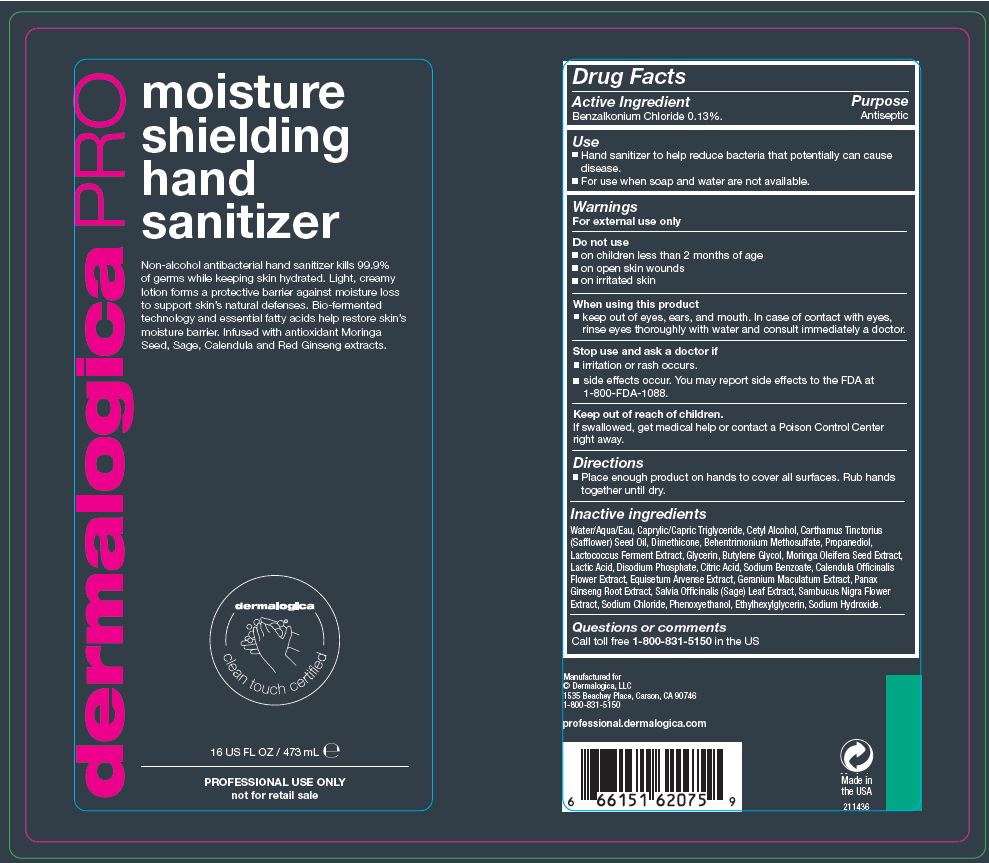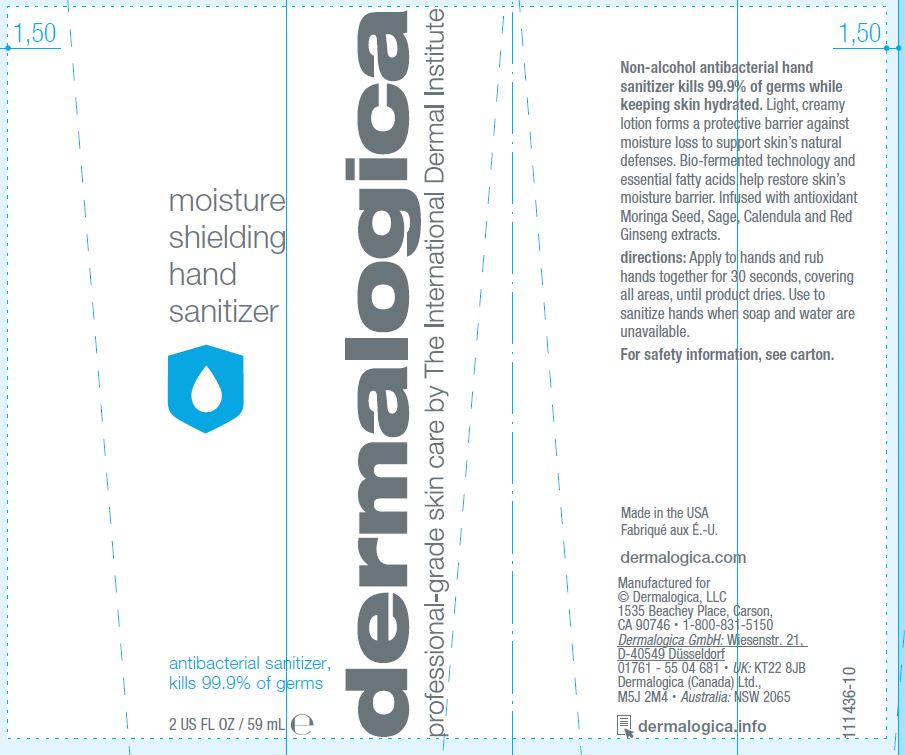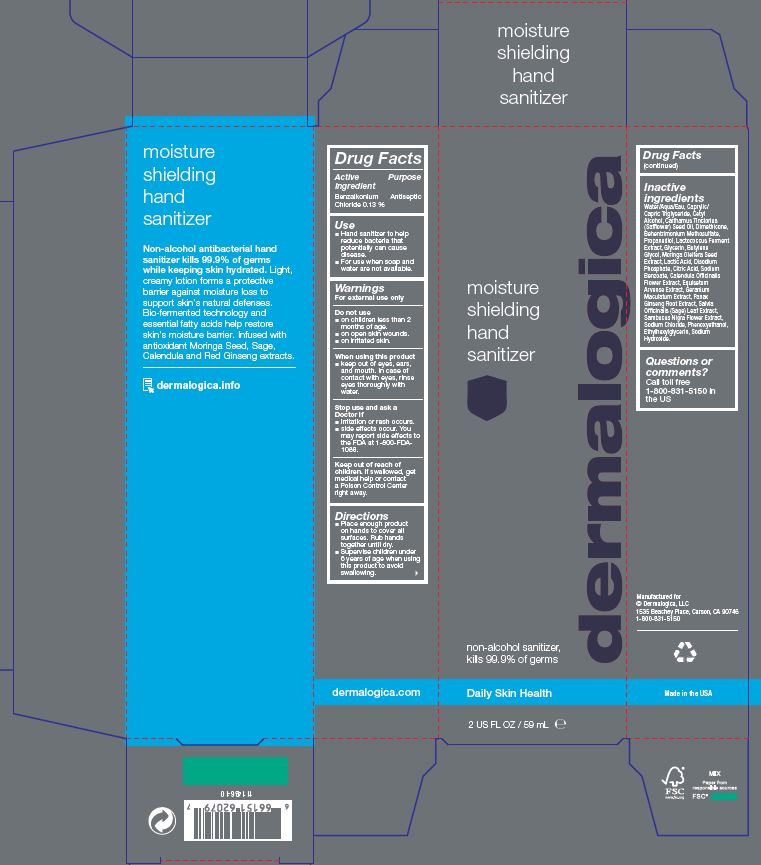 DRUG LABEL: moisture shielding hand sanitizer
NDC: 68479-209 | Form: LIQUID
Manufacturer: Dermalogica, LLC
Category: otc | Type: HUMAN OTC DRUG LABEL
Date: 20200814

ACTIVE INGREDIENTS: BENZALKONIUM CHLORIDE 0.13 g/100 mL
INACTIVE INGREDIENTS: WATER; MEDIUM-CHAIN TRIGLYCERIDES; CETYL ALCOHOL; SAFFLOWER OIL; DIMETHICONE; BEHENTRIMONIUM METHOSULFATE; PROPANEDIOL; LACTOCOCCUS LACTIS; GLYCERIN; BUTYLENE GLYCOL; MORINGA OLEIFERA SEED; LACTIC ACID; SODIUM PHOSPHATE, DIBASIC; ANHYDROUS CITRIC ACID; SODIUM BENZOATE; CALENDULA OFFICINALIS FLOWER; EQUISETUM ARVENSE BRANCH; GERANIUM MACULATUM ROOT; ASIAN GINSENG; SAGE; SAMBUCUS NIGRA FLOWER; SODIUM CHLORIDE; PHENOXYETHANOL; ETHYLHEXYLGLYCERIN; SODIUM HYDROXIDE

dermalogica
moisture shielding hand sanitizer

Active Ingredient

Benzalkonium Chloride 0.13%

Purpose

Antiseptic

Use

- Hand sanitizer to help reduce bacteria that potentially can cause disease.
- For use when soap and water are not available.

Warnings

For external use only.

Do not use

- on children less than 2 months of age
- on open skin wounds
- on irritated skin

When using this product

keep out of eyes, ears, and mouth. In case of contact with eyes, rinse eyes thoroughly with water.

Stop use and ask a doctor if

- irritation or rash occurs.
- side effects occur. You may report side effects to the FDA at 1-800-FDA-1088

Keep out of reach of children. If swallowed, get medical help or contact a Poison Control Center right away.

Directions

- Place enough product on hands to cover all surfaces. Rub hands together until dry.
- Supervise children under 6 years of age when using this product to avoid swallowing.

Inactive Ingredients

Water/Aqua/Eau, Caprylic/Capric Triglyceride, Cetyl Alcohol, Carthamus Tinctorius (Safflower) Seed Oil, Dimethicone, Behentrimonium Methosulfate, Propanediol, Lactococcus Ferment Extract, Glycerin, Butylene Glycol, Moringa Oleifera Seed Extract, Lactic Acid, Disodium Phosphate, Citric Acid, Sodium Benzoate, Calendula Officinalis Flower Extract, Equisetum Arvense Extract, Geranium Maculatum Extract, Panax Ginseng Root Extract, Salvia Officinalis (Sage) Leaf Extract, Sambucus Nigra Flower Extract,
Sodium Chloride, Phenoxyethanol, Ethylhexylglycerin, Sodium Hydroxide.

Questions or comments?

Call toll free 1-800-831-5150 in the US

Dermalogica - moisutre shielding hand sanitizer - 59 mL

Dermalogica

moisture shielding hand sanitizer

non-alcohol sanitizer,

kills 99.9% of germs

Daily Skin Health

2 US FL OZ / 59 mL

[Drug Facts Table]

Non-alcohol antibacterial hand sanitizer kills 99.9% of germs while keeping skin hydrated. Light, creamy lotion forms a protective barrier against mositure loss to support skin's natural defenses.

Bio-fermented technology and essential fatty acids help restore skin's moisture barrier. Infused with antioxidant Moringa Seed, Sage, Calendula and Red Ginseng extracts.

dermalogica.info

Manufactured for

Dermalogica, LLC

1535 Beachey Place, Carson, CA 90746

1-800-831-5150

Made in USA

Dermalogica

moisture shielding hand sanitizer

antibacterial sanitizer,

kills 99.9% of germs

2 US FL OZ / 59 mL

Non-alcohol antibacterial hand sanitizer kills 99.9% of germs while keeping skin hydrated. Light, creamy lotion forms a protective barrier against mositure loss to support skin's natural defenses.

Bio-fermented technology and essential fatty acids help restore skin's moisture barrier. Infused with antioxidant Moringa Seed, Sage, Calendula and Red Ginseng extracts.

directions: Apply to hands and rub hands together for 30 seconds, covering all areas, until product dries. Use to sanitize hands when soap and water are unavailable.

For safety information, see carton.

Made in USA

Fabrique aux EU

dermalogica.com

Manufactured for

Dermalogica, LLC

1535 Beachey Place, Carson, CA 90746

1-800-831-5150

Dermalogica GmbH: Wiesenstr. 21

D-40549 Dusseldorf

01761-55 04 681 UK: KT22 8JB

Dermalogica (Canada) Ltd.,

M5J 2M4

Australia: NSW 2065

Dermalogica PRO - moisutre shielding hand sanitizer - 473 mL

Dermalogica PRO

moisture shielding hand sanitizer

Non-alcohol antibacterial hand sanitizer kills 99.9% of germs while keeping skin hydrated. Light, creamy lotion forms a protective barrier against mositure loss to support skin's natural defenses. Bio-fermented technology and essential fatty acids help restore skin's moisture barrier. Infused with antioxidant Moringa Seed, Sage, Calendula and Red Ginseng extracts.

dermalogica clean touch certified

16 US FL OZ / 473 mL

PROFESSIONAL USE ONLY

not for retail sale

[Drug Facts Table]

Manufactured for

Dermalogica, LLC

1535 Beachey Place, Carson, CA 90746

1-800-831-5150

professional.dermalogica.com

Made in USA